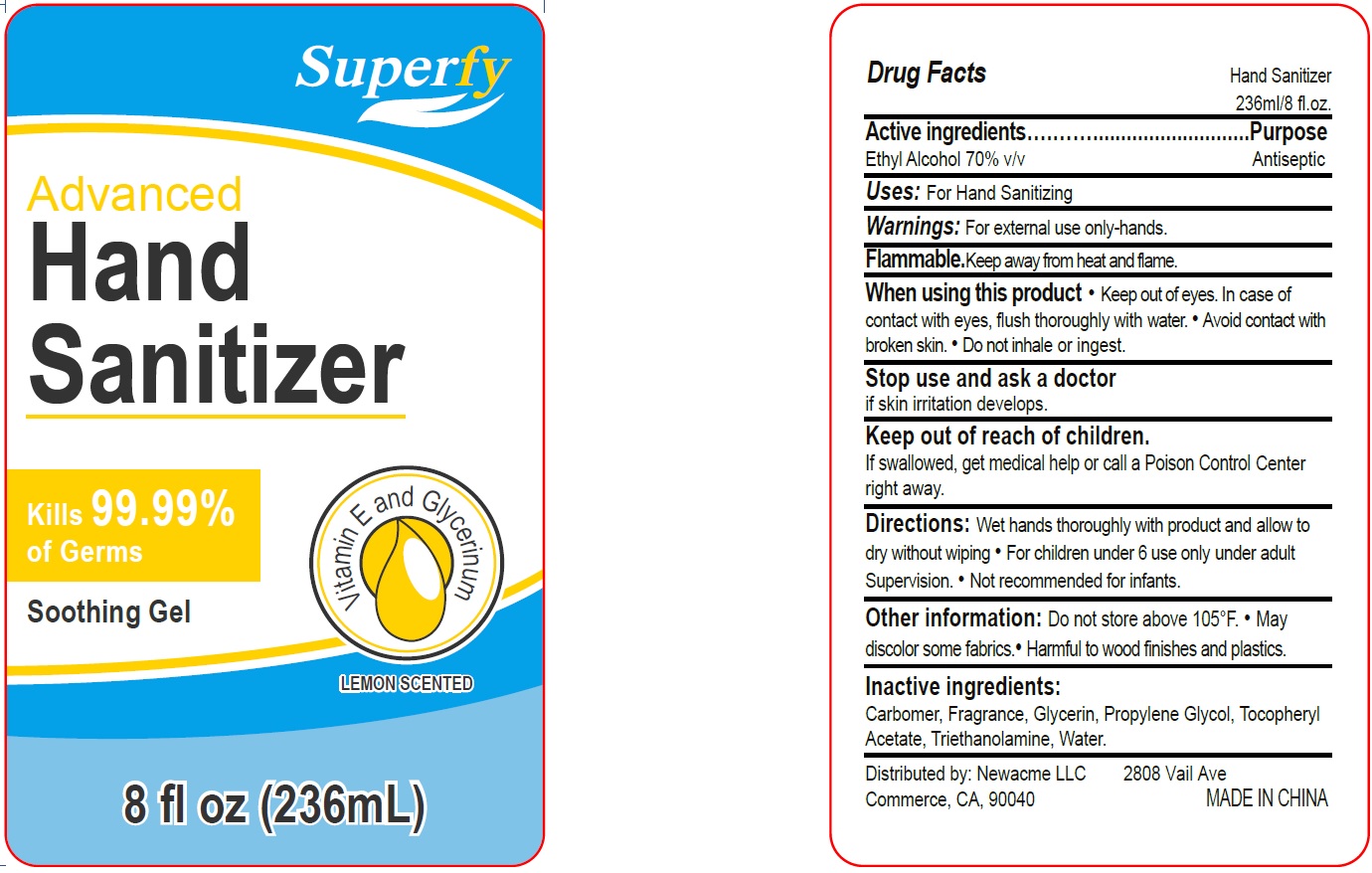 DRUG LABEL: Hand Sanitizer
NDC: 70412-192 | Form: GEL
Manufacturer: Zhejiang Ayan Biotech Co.,Ltd.
Category: otc | Type: HUMAN OTC DRUG LABEL
Date: 20231106

ACTIVE INGREDIENTS: ALCOHOL 0.7 mL/1 mL
INACTIVE INGREDIENTS: CARBOMER HOMOPOLYMER, UNSPECIFIED TYPE; GLYCERIN; PROPYLENE GLYCOL; .ALPHA.-TOCOPHEROL ACETATE; TROLAMINE; WATER

Hand Sanitizer

Active Ingredients

Ethyl Alcohol 70% v/v

Purpose

Antiseptic

Uses:

For Hand Sanitizing

Warnings:

For external use only-hands.

Keep away from heat and flame. Flammable.

When using this product

• Keep out of eyes. In case of contact with eyes, flush thoroughly with water. • Avoid contact with broken skin. • Do not inhale or ingest.

Stop use and ask a doctor

if skin irritation develops.

Keep out of reach of children.

If swallowed, get medical help or call a Poison Control Center right away.

Directions:

Wet hands thoroughly with product and allow to dry without wiping • For children under 6 use only under adult Supervision. • Not recommended for infants.

Other Information:

Do not store above 105°F. • May .• discolor some fabrics Harmful to wood finishes and plastics.

Inactive Ingredients:

Carbomer, Fragrance, Glycerin, Propylene Glycol, Tocopheryl ACetate, Triethanomalime, Water.